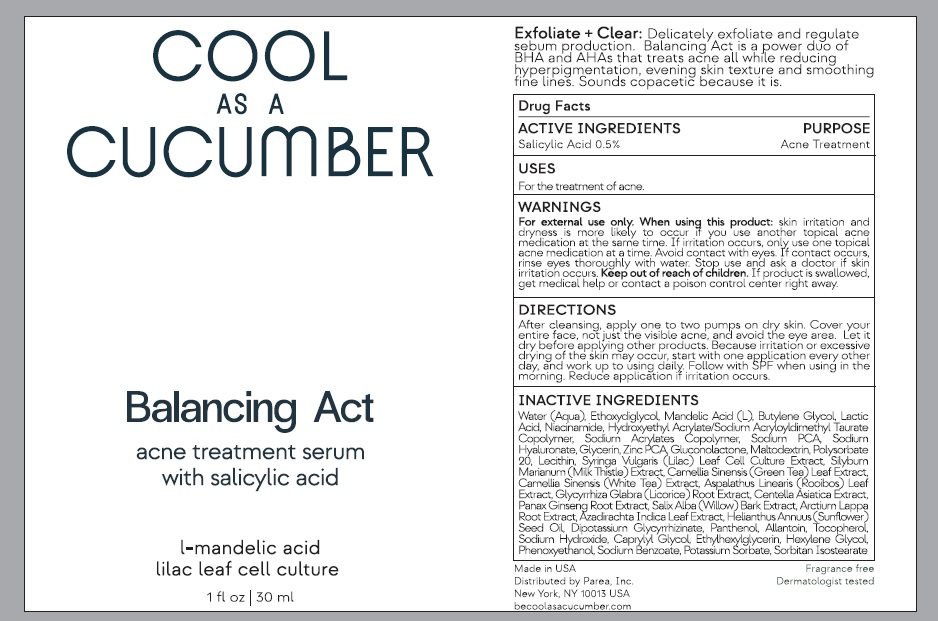 DRUG LABEL: Balancing Act
NDC: 83360-001 | Form: LIQUID
Manufacturer: Parea, Inc.
Category: otc | Type: HUMAN OTC DRUG LABEL
Date: 20230405

ACTIVE INGREDIENTS: SALICYLIC ACID 0.5 g/100 mL
INACTIVE INGREDIENTS: WATER; DIETHYLENE GLYCOL MONOETHYL ETHER; MANDELIC ACID; BUTYLENE GLYCOL; LACTIC ACID, UNSPECIFIED FORM; NIACINAMIDE; HYDROXYETHYL ACRYLATE/SODIUM ACRYLOYLDIMETHYL TAURATE COPOLYMER (100000 MPA.S AT 1.5%); SODIUM ACRYLATES CROSSPOLYMER-2; SODIUM PYRROLIDONE CARBOXYLATE; HYALURONATE SODIUM; GLYCERIN; ZINC PIDOLATE; GLUCONOLACTONE; MALTODEXTRIN; POLYSORBATE 20; LECITHIN, SOYBEAN; SYRINGA VULGARIS POLLEN; MILK THISTLE; GREEN TEA LEAF; WHITE TEA; ASPALATHUS LINEARIS LEAF; GLYCYRRHIZA GLABRA; CENTELLA ASIATICA TRITERPENOIDS; ASIAN GINSENG; SALIX ALBA BARK; ARCTIUM LAPPA ROOT; AZADIRACHTA INDICA LEAF; SUNFLOWER OIL; GLYCYRRHIZINATE DIPOTASSIUM; PANTHENOL; ALLANTOIN; TOCOPHEROL; SODIUM HYDROXIDE; CAPRYLYL GLYCOL; ETHYLHEXYLGLYCERIN; HEXYLENE GLYCOL; PHENOXYETHANOL; SODIUM BENZOATE; POTASSIUM SORBATE; SORBITAN ISOSTEARATE

Active ingredient

Salicylic acid 0.5%

Purpose

Acne treatment

Uses

For the treatment of acne.

Warnings

For external use only.

When using this product : skin irritation and dryness is more likely to occur if you use another topical acne medication at the same time. If

irritation occurs, only use one topical acne medication at a time. Avoid contact with eyes. If contact occurs, rinse eyes thoroughly with water.

Stop use and ask doctor if skin irritation occurs.

Keep out of reach of children. If product is swallowed get medical help or contact a poison control center right away.

Direction

After cleansing, apply one to two pumps on dry skin. Cover your entire face, not just the visible acne, and avoid the eye area. Let it dry before applying other products. Because irritation or excessive drying of the skin may occur, start with one application every other day, and work up to using daily. Follow with SPF when using in the morning. Reduce application if irritation occurs.

Inactive ingredients

water, diethylene glycol monoethyl ether, mandelic acid, butylene glycol, lactic acid, unspecified form, niacinamide, hydroxyethyl acrylate/sodium acryloyldimethyl taurate copolymer(100000 mpa.s at 1.5%), sodium acrylates crosspolymer-2, sodium pyrrolidone carboxylate, hyaluronate sodium, glycerin, zinc pidolate, gluconolactone, maltodextrin, polysorbate 20, lecithin, soybean, syringa vulgaris pollen, milk thistle, green tea leaf, white tea, aspalathus linearis leaf, glycyrrhiza glabra, centella asiatica triterpenoids, asian ginseng, salix alba bark, arctium lappa root, azadirachta indica leaf, sunflower oil, glycyrrhizinate dipotassium, panthenol, allantoin, tocopherol, sodium hydroxide, caprylyl glycol, ethylhexylglycerin, hexylene glycol, phenoxyethanol, sodium benzoate, potassium sorbate, sorbitan isostearateonic

Other information

Made in USA

Distributed by Parea, Inc.

New York, NY 10013 USA

becoolasacucumber.com